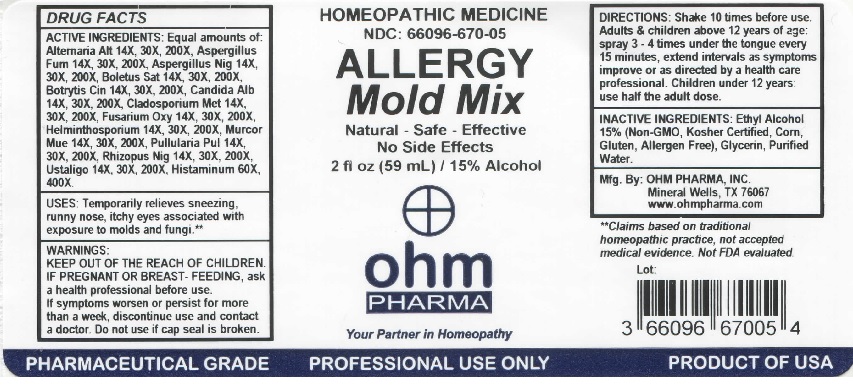 DRUG LABEL: OHM Allergy Mold Mix
NDC: 66096-670 | Form: LIQUID
Manufacturer: OHM PHARMA INC.
Category: homeopathic | Type: HUMAN OTC DRUG LABEL
Date: 20211229

ACTIVE INGREDIENTS: ALTERNARIA ALTERNATA 14 [hp_X]/59 mL; ASPERGILLUS FUMIGATUS 14 [hp_X]/59 mL; ASPERGILLUS NIGER VAR. NIGER 14 [hp_X]/59 mL; BOLETUS SATANAS FRUITING BODY 14 [hp_X]/59 mL; BOTRYTIS CINEREA 14 [hp_X]/59 mL; CANDIDA ALBICANS 14 [hp_X]/59 mL; PASSALORA FULVA 14 [hp_X]/59 mL; FUSARIUM OXYSPORUM 14 [hp_X]/59 mL; COCHLIOBOLUS SATIVUS 14 [hp_X]/59 mL; AUREOBASIDIUM PULLULANS VAR. PULLUTANS 14 [hp_X]/59 mL; RHIZOPUS STOLONIFER 14 [hp_X]/59 mL; USTILAGO MAYDIS 14 [hp_X]/59 mL; HISTAMINE DIHYDROCHLORIDE 60 [hp_X]/59 mL
INACTIVE INGREDIENTS: ALCOHOL; GLYCERIN; WATER

OHM Allergy Mold Mix

ACTIVE INGREDIENT

ACTIVE INGREDIENTS: Equal amounts of: Alternaria Alt 14X, 30X, 200X, Aspergillus Fum 14X, 30X, 200X, Aspergillus Nig 14X, 30X, 200X, Boletus Sat 14X, 30X, 200X, Botrytis Cin 14X, 30X, 200X, Candida Alb 14X, 30X, 200X, Cladosporium Met 14X, 30X, 200X, Fusarium Oxy 14X, 30X, 200X, Helminthosporium 14X, 30X, 200X, Murcor Mue 14X, 30X, 200X, Pullularia Pul 14X, 30X, 200X, Rhizopus Nig 14X, 30X, 200X, Ustaligo 14X, 30X, 200X, Histaminum 60X, 400X.

INDICATIONS AND USAGE

USES: Temporarily relieves sneezing, runny nose, itchy eyes associated with exposure to molds and fungi.**

**Claims based on traditional homeopathic practice, not accepted medical evidence. Not FDA evaluated.

WARNINGS

WARNINGS: IF PREGNANT OR BREAST-FEEDING, ask a health professional before use. If symptoms worsen or persist for more than a week, discontinue use and contact a doctor.

- Keep out of reach of children.

DOSAGE AND ADMINISTRATION

DIRECTIONS: Shake 10 times before use. Adults & children above 12 years of age: spray 3-4 times under the tongue every 15 minutes, extend intervals as symptoms improve or as directed by a health care professional. Children under 12 years: use half the adult dose.

Do not use if cap seal is broken.

INACTIVE INGREDIENT

INACTIVE INGREDIENTS: Ethy Alcohol 15% (Non-GMO, Kosher Certified, Corn, Gluten, Allergen Free), Glycerin, Purified Water.

QUESTIONS

Mfg. By: OHM PHARMA, INC. Mineral Wells, TX 76067

www.ohmpharma.com

PACKAGE LABEL

HOMEOPATHIC MEDICINE

NDC: 66096-670-05

ALLERGY

Mold Mix

Natural - Safe - Effective

No Side Effects

2 fl oz (59 mL) / 15% Alcohol

PURPOSE

Temporarily relieves sneezing,

runny nose, itchy eyes, associated with

exposure to molds and fungi.**